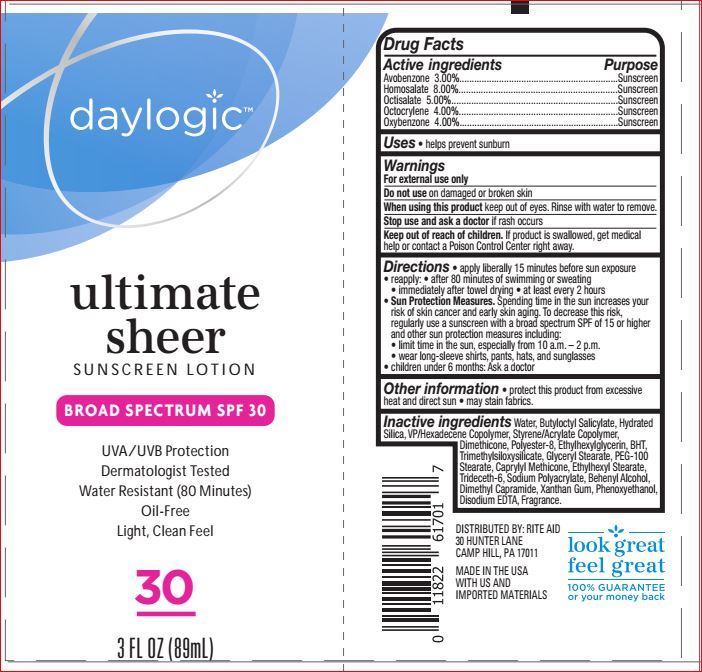 DRUG LABEL: Ultimate Sheer  Sunscreen SPF 30
NDC: 11822-1238 | Form: LOTION
Manufacturer: Rite Aid
Category: otc | Type: HUMAN OTC DRUG LABEL
Date: 20180622

ACTIVE INGREDIENTS: Avobenzone 3 g/100 mL; Homosalate 8 g/100 mL; Octisalate 5 g/100 mL; Octocrylene 4 g/100 mL; Oxybenzone 4 g/100 mL
INACTIVE INGREDIENTS: DOCOSANOL; BUTYLATED HYDROXYTOLUENE; Butyloctyl Salicylate; CAPRYLYL TRISILOXANE; Dimethicone; Dimethyl Capramide; EDETATE DISODIUM ANHYDROUS; Ethylhexyl Stearate; Ethylhexylglycerin; GLYCERYL MONOSTEARATE; Hydrated Silica; PEG-100 Stearate; Phenoxyethanol; POLYESTER-8 (1400 MW, CYANODIPHENYLPROPENOYL CAPPED); Trideceth-6; Water; Xanthan Gum

Drug Facts

Active ingredients Purpose

Avobenzone - 3.00%
Homosalate - 8.00%
Octisalate - 5.00%
Octocrylene - 4.00%
Oxybenzone - 4.00% Sunscreen

INDICATIONS AND USAGE

- helps prevent sunburn

Warnings

For external use only

Do not use on damaged or broken skin
When using this product keep out of eyes. Rinse with water to remove.
Stop use and ask a doctor if rash occurs
Keep out of reach of children. If product is swallowed, get medical help or contact a Poison Control Center right away.

Directions

applyliberally and spread evenly by hand 15 minutes before sun exposure
• reapply: • after 80 minutes of swimming or sweating
• immediately after towel drying • at least every 2 hours
• Sun Protection Measures. Spending time in the sun
increases your risk of skin cancer and early skin aging.
To decrease this risk, regularly use a sunscreen with a
broad spectrum SPF of 15 or higher and other sun
protection measures including:
• limit time in the sun, especially from 10 a.m. – 2 p.m.
• wear long-sleeve shirts, pants, hats, and sunglasses
• children under 6 months: Ask a doctor

Inactive ingredients

Behenyl Alcohol
BHT
Butyloctyl Salicylate
Caprylyl Methicone
Dimethicone
Dimethyl Capramide
Disodium EDTA
Ethylhexyl Stearate
Ethylhexylglycerin
Fragrance
Glyceryl Stearate
Hydrated Silica
PEG-100 Stearate
Phenoxyethanol
Polyester-8
Sodium Polyacrylate
Styrene/Acrylate Copolymer
Trideceth-6
Trimethylsiloxysilicate
VP/Hexadecene Copolymer
Water
Xanthan Gum